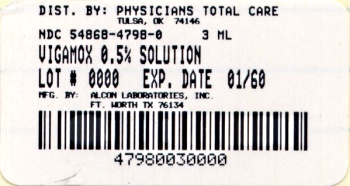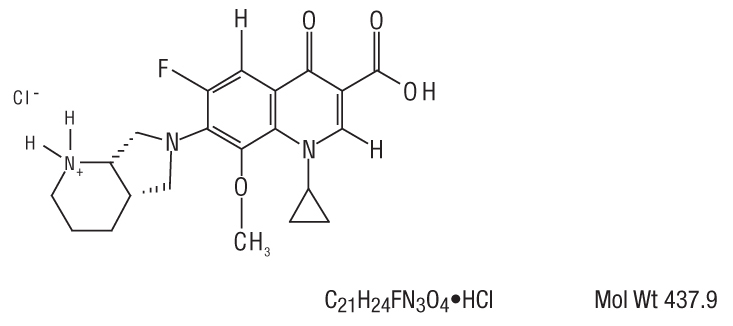 DRUG LABEL: VIGAMOX 
NDC: 54868-4798 | Form: SOLUTION
Manufacturer: Physicians Total Care, Inc.
Category: prescription | Type: HUMAN PRESCRIPTION DRUG LABEL
Date: 20111107

ACTIVE INGREDIENTS: MOXIFLOXACIN HYDROCHLORIDE 5 mg/1 mL
INACTIVE INGREDIENTS: BORIC ACID; SODIUM CHLORIDE; WATER; HYDROCHLORIC ACID; SODIUM HYDROXIDE

HIGHLIGHTS OF PRESCRIBING INFORMATION

These highlights do not include all the information needed to use VIGAMOX® Solution safely and effectively. See full prescribing information for VIGAMOX® Solution.
VIGAMOX® (moxifloxacin hydrochloride ophthalmic solution) 0.5% as base
Sterile topical ophthalmic solution
Initial U.S. Approval 1999

1 INDICATIONS AND USAGE

VIGAMOX® solution is a topical fluoroquinolone anti-infective indicated for the treatment of bacterial conjunctivitis caused by susceptible strains of the following organisms:

Corynebacterium species*, Micrococcus luteus*, Staphylococcus aureus, Staphylococcus epidermidis, Staphylococcus haemolyticus, Staphylococcus hominis, Staphylococcus warneri*, Streptococcus pneumoniae, Streptococcus viridans group, Acinetobacter lwoffii*, Haemophilus influenzae, Haemophilus parainfluenzae*, Chlamydia trachomatis

*Efficacy for this organism was studied in fewer than 10 infections. (1)

2 DOSAGE AND ADMINISTRATION

Instill one drop in the affected eye 3 times a day for 7 days. (2)

3 DOSAGE FORMS AND STRENGTHS

4 mL bottle filled with 3 mL sterile ophthalmic solution of moxifloxacin hydrochloride, 0.5% as base. (3)

4 CONTRAINDICATIONS

VIGAMOX® solution is contraindicated in patients with a history of hypersensitivity to moxifloxacin, to other quinolones, or to any of the components in this medication. (4)

5 WARNINGS AND PRECAUTIONS

- Topical ophthalmic use only. (5.1)
- Hypersensitivity and anaphylaxis have been reported with systemic use of moxifloxacin. (5.2)
- Prolonged use may result in overgrowth of non-susceptible organisms, including fungi. (5.3)
- Patients should not wear contact lenses if they have signs or symptoms of bacterial conjunctivitis. (5.4)

6 ADVERSE REACTIONS

The most frequently reported ocular adverse events were conjunctivitis, decreased visual acuity, dry eye, keratitis, ocular discomfort, ocular hyperemia, ocular pain, ocular pruritus, subconjunctival hemorrhage, and tearing. These events occurred in approximately 1-6% of patients. (6)
To report SUSPECTED ADVERSE REACTIONS, contact Alcon Laboratories, Inc. at 1-800-757-9195 or FDA at 1-800-FDA-1088 or www.fda.gov/medwatch.

FULL PRESCRIBING INFORMATION

1 INDICATIONS AND USAGE

VIGAMOX® solution is indicated for the treatment of bacterial conjunctivitis caused by susceptible strains of the following organisms:

Corynebacterium species*
Micrococcus luteus*
Staphylococcus aureus
Staphylococcus epidermidis
Staphylococcus haemolyticus
Staphylococcus hominis
Staphylococcus warneri*
Streptococcus pneumoniae
Streptococcus viridans group
Acinetobacter lwoffii*
Haemophilus influenzae
Haemophilus parainfluenzae*
Chlamydia trachomatis

*Efficacy for this organism was studied in fewer than 10 infections.

2 DOSAGE AND ADMINISTRATION

Instill one drop in the affected eye 3 times a day for 7 days.

3 DOSAGE FORMS AND STRENGTHS

4 mL bottle filled with 3 mL sterile ophthalmic solution of moxifloxacin hydrochloride, 0.5% as base.

4 CONTRAINDICATIONS

VIGAMOX® solution is contraindicated in patients with a history of hypersensitivity to moxifloxacin, to other quinolones, or to any of the components in this medication.

5 WARNINGS AND PRECAUTIONS

5.1 Topical Ophthalmic Use Only

NOT FOR INJECTION. VIGAMOX® solution is for topical ophthalmic use only and should not be injected subconjunctivally or introduced directly into the anterior chamber of the eye.

5.2 Hypersensitivity Reaction

In patients receiving systemically administered quinolones, including moxifloxacin, serious and occasionally fatal hypersensitivity (anaphylactic) reactions have been reported, some following the first dose. Some reactions were accompanied by cardiovascular collapse, loss of consciousness, angioedema (including laryngeal, pharyngeal or facial edema), airway obstruction, dyspnea, urticaria, and itching. If an allergic reaction to moxifloxacin occurs, discontinue use of the drug. Serious acute hypersensitivity reactions may require immediate emergency treatment. Oxygen and airway management should be administered as clinically indicated.

5.3 Growth of Resistant Organisms with Prolonged Use

As with other anti-infectives, prolonged use may result in overgrowth of non-susceptible organisms, including fungi. If superinfection occurs, discontinue use and institute alternative therapy. Whenever clinical judgment dictates, the patient should be examined with the aid of magnification, such as slit-lamp biomicroscopy, and, where appropriate, fluorescein staining.

5.4 Avoidance of Contact Lens Wear

Patients should be advised not to wear contact lenses if they have signs or symptoms of bacterial conjunctivitis.

6 ADVERSE REACTIONS

Because clinical trials are conducted under widely varying conditions, adverse reaction rates observed in the clinical trials of a drug cannot be directly compared to the rates in the clinical trials of another drug and may not reflect the rates observed in practice.

The most frequently reported ocular adverse events were conjunctivitis, decreased visual acuity, dry eye, keratitis, ocular discomfort, ocular hyperemia, ocular pain, ocular pruritus, subconjunctival hemorrhage, and tearing. These events occurred in approximately 1-6% of patients.

Nonocular adverse events reported at a rate of 1-4% were fever, increased cough, infection, otitis media, pharyngitis, rash, and rhinitis.

7 DRUG INTERACTIONS

Drug-drug interaction studies have not been conducted with VIGAMOX® solution. In vitro studies indicate that moxifloxacin does not inhibit CYP3A4, CYP2D6, CYP2C9, CYP2C19, or CYP1A2, indicating that moxifloxacin is unlikely to alter the pharmacokinetics of drugs metabolized by these cytochrome P450 isozymes.

8 USE IN SPECIFIC POPULATIONS

8.1 Pregnancy

Pregnancy Category C.
Teratogenic Effects: Moxifloxacin was not teratogenic when administered to pregnant rats during organogenesis at oral doses as high as 500 mg/kg/day (approximately 21,700 times the highest recommended total daily human ophthalmic dose); however, decreased fetal body weights and slightly delayed fetal skeletal development were observed. There was no evidence of teratogenicity when pregnant Cynomolgus monkeys were given oral doses as high as 100 mg/kg/day (approximately 4,300 times the highest recommended total daily human ophthalmic dose). An increased incidence of smaller fetuses was observed at 100 mg/kg/day.

Since there are no adequate and well-controlled studies in pregnant women, VIGAMOX® solution should be used during pregnancy only if the potential benefit justifies the potential risk to the fetus.

8.3 Nursing Mothers

Moxifloxacin has not been measured in human milk, although it can be presumed to be excreted in human milk. Caution should be exercised when VIGAMOX® solution is administered to a nursing mother.

8.4 Pediatric Use

The safety and effectiveness of VIGAMOX® solution in infants below 1 year of age have not been established.

There is no evidence that the ophthalmic administration of VIGAMOX® solution has any effect on weight bearing joints, even though oral administration of some quinolones has been shown to cause arthropathy in immature animals.

8.5 Geriatric Use

No overall differences in safety and effectiveness have been observed between elderly and younger patients.

11 DESCRIPTION

VIGAMOX® (moxifloxacin hydrochloride ophthalmic solution) 0.5% is a sterile solution for topical ophthalmic use. Moxifloxacin hydrochloride is an 8-methoxy fluoroquinolone anti-infective, with a diazabicyclononyl ring at the C7 position.

Chemical Name:
1-Cyclopropyl-6-fluoro-1,4-dihydro-8-methoxy-7-[(4aS,7aS)-octahydro-6H-pyrrolol[3,4-b]pyridin-6-yl]-4-oxo-3-quinoline carboxylic acid, monohydrochloride. Moxifloxacin hydrochloride is a slightly yellow to yellow crystalline powder. Each mL of VIGAMOX® solution contains 5.45 mg moxifloxacin hydrochloride, equivalent to 5 mg moxifloxacin base.

Contains: Active: Moxifloxacin 0.5% (5 mg/mL); Inactives: Boric acid, sodium chloride, and purified water. May also contain hydrochloric acid/sodium hydroxide to adjust pH to approximately 6.8.

VIGAMOX® solution is an isotonic solution with an osmolality of approximately 290 mOsm/kg.

12 CLINICAL PHARMACOLOGY

12.1 Mechanism of Action

Moxifloxacin is a member of the fluoroquinolone class of anti-infective drugs (See 12.4 Microbiology).

12.3 Pharmacokinetics

Plasma concentrations of moxifloxacin were measured in healthy adult male and female subjects who received bilateral topical ocular doses of VIGAMOX® solution 3 times a day. The mean steady-state Cmax (2.7 ng/mL) and estimated daily exposure AUC (45 ng•hr/mL) values were 1,600 and 1,000 times lower than the mean Cmax and AUC reported after therapeutic 400 mg doses of moxifloxacin. The plasma half-life of moxifloxacin was estimated to be 13 hours.

12.4 Microbiology

The antibacterial action of moxifloxacin results from inhibition of the topoisomerase II (DNA gyrase) and topoisomerase IV. DNA gyrase is an essential enzyme that is involved in the replication, transcription and repair of bacterial DNA. Topoisomerase IV is an enzyme known to play a key role in the partitioning of the chromosomal DNA during bacterial cell division.

The mechanism of action for quinolones, including moxifloxacin, is different from that of macrolides, aminoglycosides, or tetracyclines. Therefore, moxifloxacin may be active against pathogens that are resistant to these antibiotics and these antibiotics may be active against pathogens that are resistant to moxifloxacin. There is no cross-resistance between moxifloxacin and the aforementioned classes of antibiotics. Cross resistance has been observed between systemic moxifloxacin and some other quinolones.

In vitro resistance to moxifloxacin develops via multiple-step mutations. Resistance to moxifloxacin occurs in vitro at a general frequency of between 1.8 x 10^-9 to < 1 x 10^-11 for Gram-positive bacteria.

Moxifloxacin has been shown to be active against most strains of the following microorganisms, both in vitro and in clinical infections as described in the INDICATIONS AND USAGE section:

Aerobic Gram-positive microorganisms:
Corynebacterium species*
Micrococcus luteus*
Staphylococcus aureus
Staphylococcus epidermidis
Staphylococcus haemolyticus
Staphylococcus hominis
Staphylococcus warneri*
Streptococcus pneumoniae
Streptococcus viridans group

Aerobic Gram-negative microorganisms:
Acinetobacter lwoffii*
Haemophilus influenzae
Haemophilus parainfluenzae*

Other microorganisms:
Chlamydia trachomatis

*Efficacy for this organism was studied in fewer than 10 infections.

The following in vitro data are also available, but their clinical significance in ophthalmic infections is unknown. The safety and effectiveness of VIGAMOX® solution in treating ophthalmological infections due to these microorganisms have not been established in adequate and well-controlled trials.

The following organisms are considered susceptible when evaluated using systemic breakpoints. However, a correlation between the in vitro systemic breakpoint and ophthalmological efficacy has not been established. The list of organisms is provided as guidance only in assessing the potential treatment of conjunctival infections. Moxifloxacin exhibits in vitro minimal inhibitory concentrations (MICs) of 2 μg/ml or less (systemic susceptible breakpoint) against most (≥ 90%) strains of the following ocular pathogens.

Aerobic Gram-positive microorganisms:
Listeria monocytogenes
Staphylococcus saprophyticus
Streptococcus agalactiae
Streptococcus mitis
Streptococcus pyogenes
Streptococcus Group C, G and F

Aerobic Gram-negative microorganisms:
Acinetobacter baumannii
Acinetobacter calcoaceticus
Citrobacter freundii
Citrobacter koseri
Enterobacter aerogenes
Enterobacter cloacae
Escherichia coli
Klebsiella oxytoca
Klebsiella pneumoniae
Moraxella catarrhalis
Morganella morganii
Neisseria gonorrhoeae
Proteus mirabilis
Proteus vulgaris
Pseudomonas stutzeri

Anaerobic microorganisms:
Clostridium perfringens
Fusobacterium species
Prevotella species
Propionibacterium acnes

Other microorganisms:
Chlamydia pneumoniae
Legionella pneumophila
Mycobacterium avium
Mycobacterium marinum
Mycoplasma pneumoniae

13 NONCLINICAL TOXICOLOGY

13.1 Carcinogenesis, Mutagenesis, Impairment of Fertility

Long-term studies in animals to determine the carcinogenic potential of moxifloxacin have not been performed. However, in an accelerated study with initiators and promoters, moxifloxacin was not carcinogenic in rats following up to 38 weeks of oral dosing at 500 mg/kg/day (approximately 21,700 times the highest recommended total daily human ophthalmic dose for a 50 kg person, on a mg/kg basis).

Moxifloxacin was not mutagenic in four bacterial strains used in the Ames Salmonella reversion assay. As with other quinolones, the positive response observed with moxifloxacin in strain TA 102 using the same assay may be due to the inhibition of DNA gyrase. Moxifloxacin was not mutagenic in the CHO/HGPRT mammalian cell gene mutation assay. An equivocal result was obtained in the same assay when v79 cells were used. Moxifloxacin was clastogenic in the v79 chromosome aberration assay, but it did not induce unscheduled DNA synthesis in cultured rat hepatocytes. There was no evidence of genotoxicity in vivo in a micronucleus test or a dominant lethal test in mice.

Moxifloxacin had no effect on fertility in male and female rats at oral doses as high as 500 mg/kg/day, approximately 21,700 times the highest recommended total daily human ophthalmic dose. At 500 mg/kg orally there were slight effects on sperm morphology (head-tail separation) in male rats and on the estrous cycle in female rats.

14 CLINICAL STUDIES

In two randomized, double-masked, multicenter, controlled clinical trials in which patients were dosed 3 times a day for 4 days, VIGAMOX® solution produced clinical cures on day 5-6 in 66% to 69% of patients treated for bacterial conjunctivitis. Microbiological success rates for the eradication of baseline pathogens ranged from 84% to 94%. Please note that microbiologic eradication does not always correlate with clinical outcome in anti-infective trials.

16 HOW SUPPLIED/STORAGE AND HANDLING

VIGAMOX® solution is supplied as a sterile ophthalmic solution in Alcon’s DROP-TAINER® dispensing system consisting of a natural low density polyethylene bottle and dispensing plug and tan polypropylene closure. Tamper evidence is provided with a shrink band around the closure and neck area of the package.

3 mL in a 4 mL bottle - NDC 54868-4798-0

Storage: Store at 2°C- 25°C (36°F - 77°F).

17 PATIENT COUNSELING INFORMATION

Patients should be advised not to touch the dropper tip to any surface to avoid contaminating the contents.

Patients should be advised not to wear contact lenses if they have signs and symptoms of bacterial conjunctivitis.

Systemically administered quinolones including moxifloxacin have been associated with hypersensitivity reactions, even following a single dose. Patients should be told to discontinue use immediately and contact their physician at the first sign of a rash or allergic reaction.

Rx Only

Licensed to Alcon by Bayer Pharma AG.
U.S. PAT. NO. 5,607,942; 6,716,830; 7,671,070
© 2003-2011 Novartis

Manufactured by
Alcon Laboratories, Inc.
Fort Worth, TX 76134 USA
9007343-1011

Additional barcode label applied by:
Physicians Total Care, Inc.
Tulsa, Oklahoma 74146

PRINCIPAL DISPLAY PANEL

NDC 54868-4798-0

STERILE

VIGAMOX®
(moxifloxacin hydrochloride
ophthalmic solution)
0.5% as base

3 mL